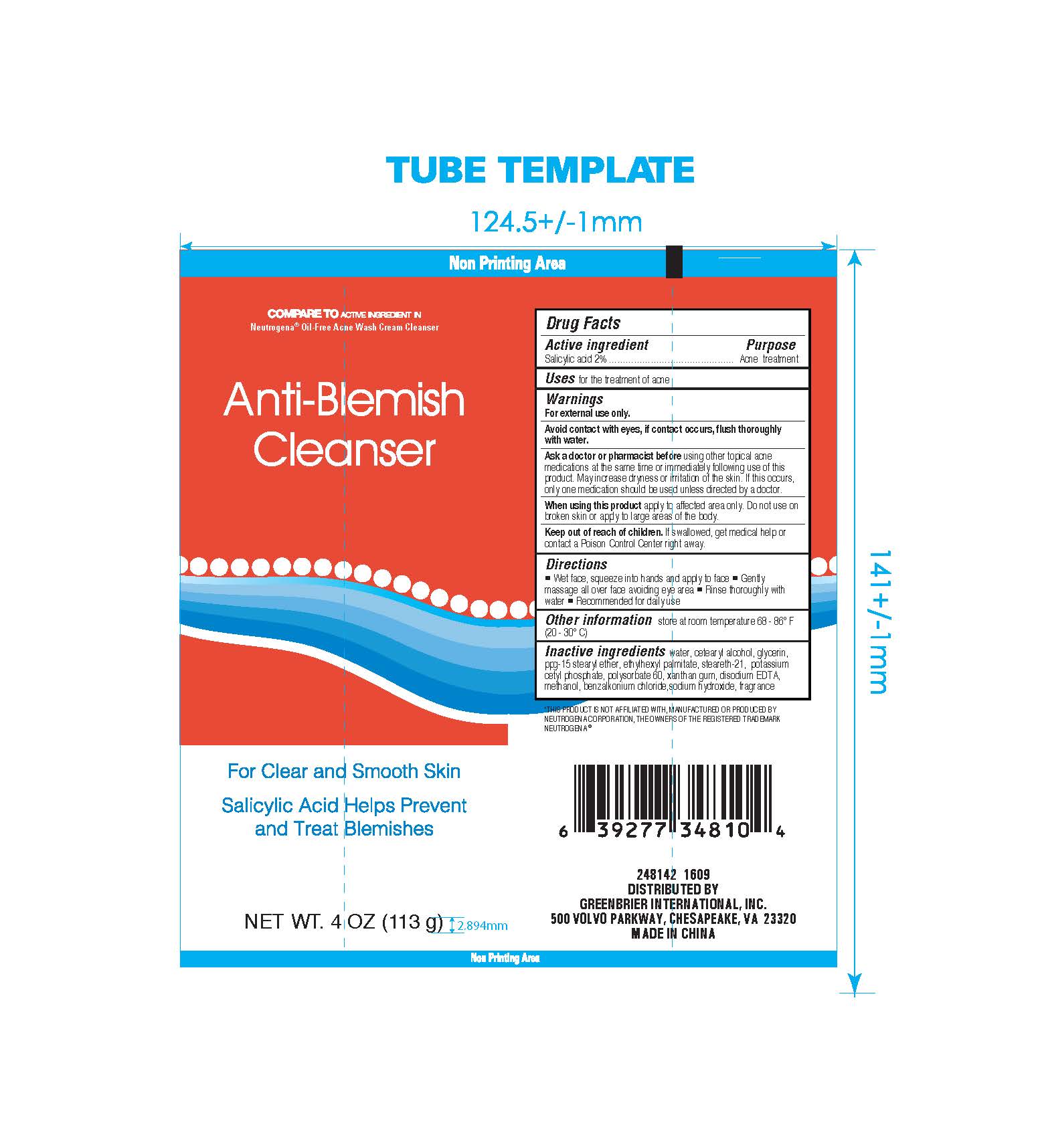 DRUG LABEL: Anti-Blemish Cleanser
NDC: 58194-054 | Form: CREAM
Manufacturer: Shanghai Weierya Daily Chemicals Factory
Category: otc | Type: HUMAN OTC DRUG LABEL
Date: 20160717

ACTIVE INGREDIENTS: SALICYLIC ACID 2 g/100 g
INACTIVE INGREDIENTS: WATER; GLYCERIN; CETOSTEARYL ALCOHOL; PPG-15 STEARYL ETHER; ETHYLHEXYL PALMITATE; POLYSORBATE 60; steareth-21; POTASSIUM CETYL PHOSPHATE; XANTHAN GUM; EDETATE DISODIUM; METHANOL, (((1-METHYL-2-(5-METHYL-3-OXAZOLIDINYL)ETHOXY)METHOXY)METHOXY)-; BENZALKONIUM CHLORIDE; SODIUM HYDROXIDE

Active ingredient

Salicylic acid 2%

Purpose

Acne treatment

INDICATIONS AND USAGE

Uses for the treatment of acne

Warnings

For external use only.

Avoid contact with eyes & lip, if contact

occurs, flush thoroughly with water.

Ask a doctor or pharmacist before using

other topical acne medications at the same time

or immediately following use of this product. May increase

dryness or irritation of the skin. If this occurs, only one

medication should be usedunless directed

by a doctor.

When using this product apply to affected

area only. Do not use on broken skin or

apply to large areas of the body.

Keep out of reach of children. If

swallowed, get medical help or contact a

Poison Control Center right away.

Directions

-Wet face, squeeze into hands and apply to face

-Gently massage all over face avoiding eye area

-Rinse thoroughly with water

-Recommended for daily use

Other information store at room

temperature 68 - 86 F (20 - 30 C)

Inactive ingredients water, cetearyl alcohol, glycerin,

ppg-15 stearyl ether, ethylhexyl palmitate, steareth-21, potassium

cetyl phosphate, polysorbate 60, xanthan gum, disodium EDTA,

methanol, benzalkonium chloride, sodium hydroxide, fragrance